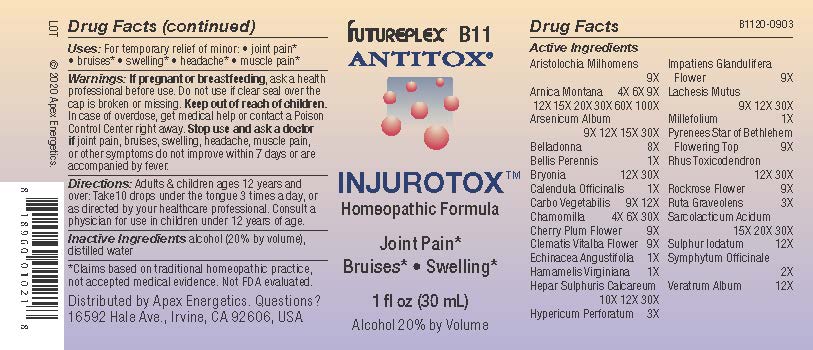 DRUG LABEL: B11
NDC: 63479-0211 | Form: SOLUTION/ DROPS
Manufacturer: Apex Energetics Inc.
Category: homeopathic | Type: HUMAN OTC DRUG LABEL
Date: 20240108

ACTIVE INGREDIENTS: ARISTOLOCHIA CYMBIFERA FLOWER 9 [hp_X]/1 mL; ARNICA MONTANA 100 [hp_X]/1 mL; ARSENIC TRIOXIDE 30 [hp_X]/1 mL; BELLIS PERENNIS 1 [hp_X]/1 mL; ACHILLEA MILLEFOLIUM 1 [hp_X]/1 mL; RUTA GRAVEOLENS FLOWERING TOP 3 [hp_X]/1 mL; LACTIC ACID, L- 30 [hp_X]/1 mL; ACTIVATED CHARCOAL 12 [hp_X]/1 mL; MATRICARIA CHAMOMILLA 30 [hp_X]/1 mL; PRUNUS CERASIFERA FLOWER 9 [hp_X]/1 mL; CLEMATIS VITALBA FLOWER 9 [hp_X]/1 mL; ECHINACEA ANGUSTIFOLIA 1 [hp_X]/1 mL; HELIANTHEMUM NUMMULARIUM FLOWER 9 [hp_X]/1 mL; COMFREY ROOT 2 [hp_X]/1 mL; VERATRUM ALBUM ROOT 12 [hp_X]/1 mL; ORNITHOGALUM UMBELLATUM FLOWERING TOP 9 [hp_X]/1 mL; TOXICODENDRON PUBESCENS LEAF 30 [hp_X]/1 mL; ATROPA BELLADONNA 8 [hp_X]/1 mL; CALENDULA OFFICINALIS FLOWERING TOP 1 [hp_X]/1 mL; HAMAMELIS VIRGINIANA ROOT BARK/STEM BARK 1 [hp_X]/1 mL; CALCIUM SULFIDE 30 [hp_X]/1 mL; LACHESIS MUTA VENOM 30 [hp_X]/1 mL; SULFUR IODIDE 12 [hp_X]/1 mL; BRYONIA ALBA ROOT 30 [hp_X]/1 mL; HYPERICUM PERFORATUM 3 [hp_X]/1 mL; IMPATIENS GLANDULIFERA FLOWER 9 [hp_X]/1 mL
INACTIVE INGREDIENTS: ALCOHOL; WATER

B11

Active Ingredients
Aristolochia Milhomens | 9X
Arnica Montana | 4X 6X 9X 12X 15X 20X 30X 60X 100X
Arsenicum Album | 9X 12X 15X 30X
Belladonna | 8X
Bellis Perennis | 1X
Bryonia | 12X 30X
Calendula Officinalis | 1X
Carbo Vegetabilis | 9X 12X
Chamomilla | 4X 6X 30X
Cherry Plum Flower | 9X
Clematis Vitalba Flower | 9X
Echinacea Angustifolia | 1X
Hamamelis Virginiana | 1X
Hepar Sulphuris Calcareum | 10X 12X 30X
Hypericum Perforatum | 3X
Impatiens Glandulifera Flower | 9X
Lachesis Mutus | 9X 12X 30X
Millefolium | 1X
Pyrenees Star Of Bethlehem Flowering Top | 9X
Rhus Toxicodendron | 12X 30X
Rockrose Flower | 9X
Ruta Graveolens | 3X
Sarcolacticum Acidum | 15X 20X 30X
Sulphur Iodatum | 12X
Symphytum Officinale | 2X
Veratrum Album | 12X

INDICATIONS AND USAGE

Uses:

For temporary relief of minor:

joint pain*

bruises*

swelling*

headache*

muscle pain*

*Claims based on traditional homeopathic practice, not accepted medical evidence. Not FDA evaluated.

WARNINGS

PREGNANCY OR BREAST FEEDING

If pregnant or breastfeeding, ask a health professional before use.

Do not use if clear seal over the cap is broken or missing.

Keep out of reach of children. In case of overdose, get medical help or contact a Poison Control Center right away.

Stop use and ask a doctor if joint pain, bruises, swelling, headache, muscle pain, or other symptoms do not improve within 7 days or are accompanied by fever.

Directions:

Adults & children ages 12 years and over: Take10 drops under the tongue 3 times a day, or as directed by your healthcare professional. Consult a physician for use in children under 12 years of age.

Inactive Ingredients

alcohol (20% by volume), distilled water

Distributed by Apex Energetics. Questions?

16592 Hale Ave., Irvine, CA 92606, USA

PACKAGE LABEL

FUTUREPLEX® B11

ANTITOX®

INJUROTOX™

Homeopathic Formula

Joint Pain*

Bruises*

Swelling*

1 fl oz (30 mL)

Alcohol 20% by Volume